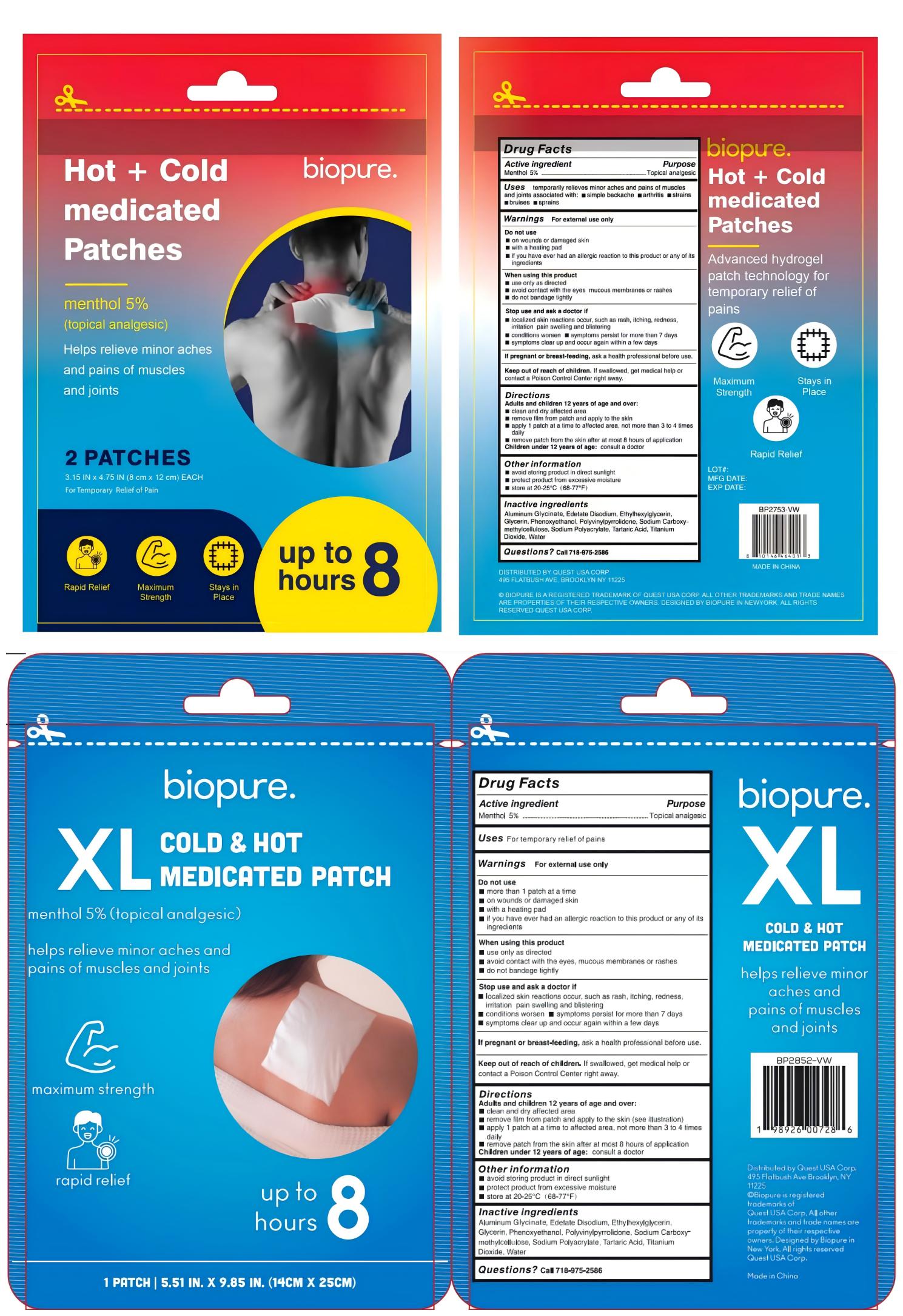 DRUG LABEL: Hot Cold Medicated Patches
NDC: 83559-003 | Form: PATCH
Manufacturer: Henan Enokon Medical Instrument Co., Ltd.
Category: otc | Type: HUMAN OTC DRUG LABEL
Date: 20250402

ACTIVE INGREDIENTS: MENTHOL 5 g/100 1
INACTIVE INGREDIENTS: GLYCERIN; CARBOXYMETHYLCELLULOSE SODIUM, UNSPECIFIED FORM; TITANIUM DIOXIDE; DIHYDROXYALUMINUM AMINOACETATE ANHYDROUS; WATER; POVIDONE; TARTARIC ACID; ETHYLHEXYLGLYCERIN; PHENOXYETHANOL; EDETATE DISODIUM; SODIUM ACRYLATE

83559-003

Active Ingredient

Menthol 5%

Purpose

Topical analgesic

Use

temporarily relieves minor aches and pains of muscles and joints associated with:■simple backache■arthritis■ strains■bruises ■sprains

Warnings

For external use only

Do not use

■ on wounds or damaged skin with a heating pad
■ if you have ever had an allergic reaction to this product or any of its ingredients

When Using

When using this product
■ use only as directed
■ avoid contact with the eyes mucous membranes or rashes ■ do not bandage tightly

Stop Use

Stop use and ask a doctor if
■ localized skin reactions occur, such as rash, itching, redness, irritation pain swelling and blistering
■ conditions worsen
■ symptoms persist for more than 7 days
■ symptoms clear up and occur again within a few days

Ask Doctor

If pregnant or breast-feeding, ask a health professional before use.

Keep Out Of Reach Of Children

If swallowed, get medical help or contact a Poison Control Center right away.

Directions

Adults and children 12 years of age and over:
■ clean and dry affected area
■ remove film from patch and apply to the skin
■ apply 1 patch at a time to affected area, not more than 3 to 4 times daily
■ remove patch from the skin after at most 8 hours of application
Children under 12 years of age: consult a doctor

Other information

■ avoid storing product in direct sunlight
■ protect product from excessive moisture
■ store at 20-25°C(68-77°F)

Inactive ingredients

Aluminum Glycinate, Edetate Disodium, Ethylhexylglycerin, Glycerin, Phenoxyethanol, Polyvinylpyrrolidone, Sodium Carboxymethylcellulose, Sodium Polyacrylate, Tartaric Acid, Titanium Dioxide, Water

Questions

Call 718-975-2586